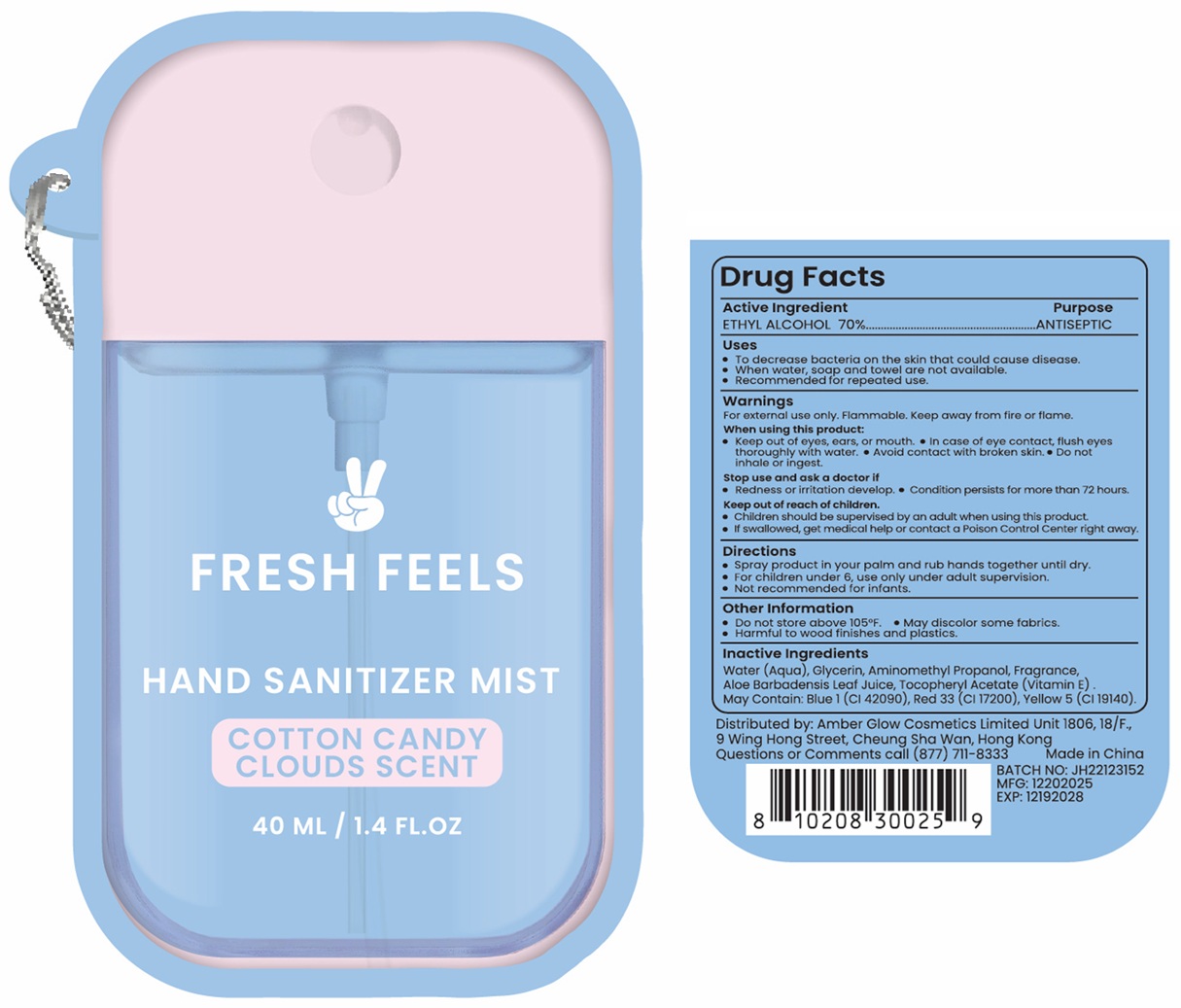 DRUG LABEL: FRESH FEELS HAND SANITIZER MIST COTTON CANDY CLOUDS SCENT
NDC: 87302-210 | Form: SPRAY
Manufacturer: Amber Glow Cosmetics Limited
Category: otc | Type: HUMAN OTC DRUG LABEL
Date: 20251226

ACTIVE INGREDIENTS: ALCOHOL 70 mL/100 mL
INACTIVE INGREDIENTS: WATER; GLYCERIN; AMINOMETHYLPROPANOL; ALOE VERA LEAF JUICE; .ALPHA.-TOCOPHEROL ACETATE; FD&C BLUE NO. 1; D&C RED NO. 33; FD&C YELLOW NO. 5

FRESH FEELS HAND SANITIZER MIST COTTON CANDY CLOUDS SCENT

Active Ingredient

ETHYL ALCOHOL 70%

Purpose

ANTISEPTIC

Uses

• To decrease bacteria on the skin that could cause disease.
• When water, soap and towel are not available.
• Recommended for repeated use.

Warnings

For external use only. Flammable. Keep away from fire or flame.

When using this product:
• Keep out of eyes, ears or mouth. • In case of eye contact, flush eyes thoroughly with water. • Avoid contact with broken skin. • Do not inhale or
ingest.

Stop use and ask a doctor if
• Redness or irritation develop. • Condition persists for more than 72 hours.

Keep out of reach of children.
• Children should be supervised by an adult when using this product.
• If swallowed, get medical help or contact a Poison Control Center right away.

Directions

• Spray product in your palm and rub hands together until dry.
• For children under 6, use only under adult supervision.
• Not recommended for infants.

Other Information

• Do not store above 105°F. • May discolor some fabrics.
• Harmful to wood finishes and plastics.

Inactive Ingredients

Water (Aqua), Glycerin, Aminomethyl Propanol, Fragrance, Aloe Barbadensis Leaf Juice, Tocopheryl Acetate (Vitamin E). May Contain: Blue 1 (Cl 42090), Red 33 (Cl 17200), Yellow 5 (Cl 19140).

Distributed by: Amber Glow Cosmetics Limited Unit 1806, 18/F.,
9 Wing Hong Street, Cheung Sha Wan, Hong Kong
Questions or Comments call (877) 711-8333

Made in China